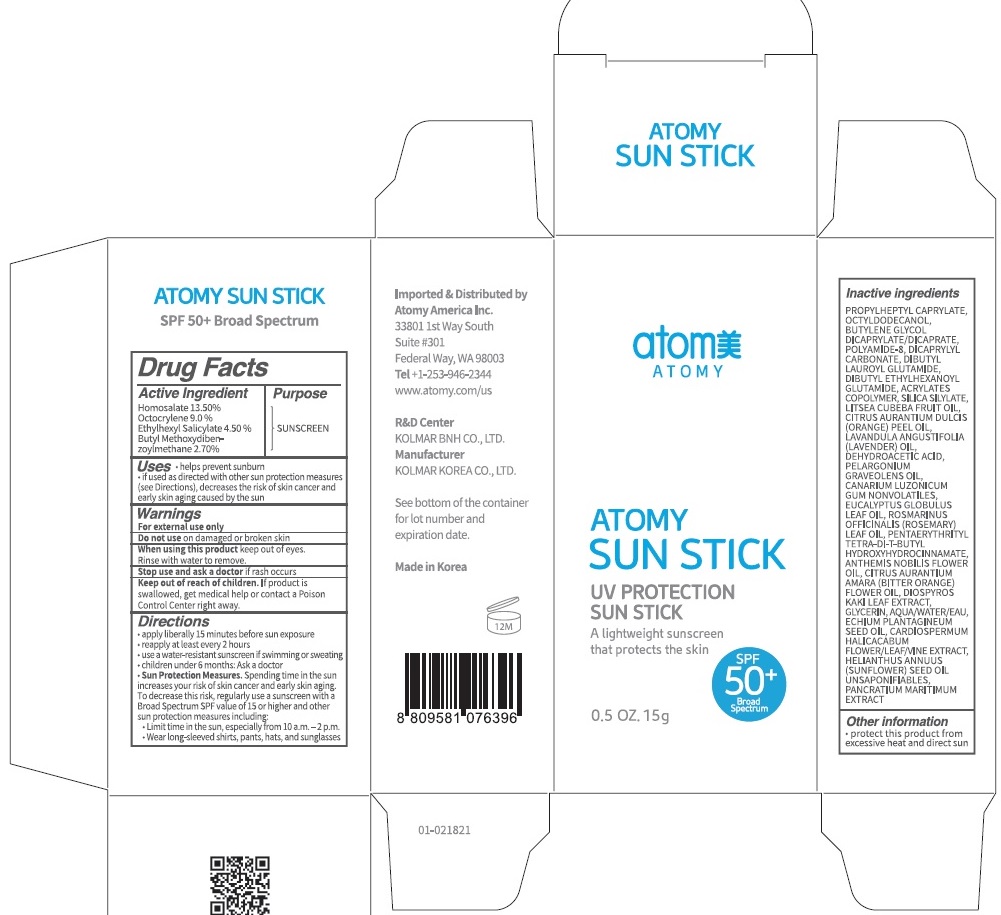 DRUG LABEL: ATOMY SUN
NDC: 52257-1390 | Form: STICK
Manufacturer: ATOMY CO., LTD.
Category: otc | Type: HUMAN OTC DRUG LABEL
Date: 20240130

ACTIVE INGREDIENTS: HOMOSALATE 2.02 g/15 g; OCTOCRYLENE 1.35 g/15 g; OCTISALATE 0.67 g/15 g; AVOBENZONE 0.40 g/15 g
INACTIVE INGREDIENTS: PROPYLHEPTYL CAPRYLATE; OCTYLDODECANOL

ACTIVE INGREDIENTS

HOMOSALATE 13.5%
OCTOCRYLENE 9.0%
ETHYLHEXYL SALICYLATE 4.5%
BUTYL METHOXYDIBENZOYLMETHANE 2.7%

INACTIVE INGREDIENTS

PROPYLHEPTYL CAPRYLATE, OCTYLDODECANOL, BUTYLENE GLYCOL DICAPRYLATE/DICAPRATE, POLYAMIDE-8, DICAPRYLYL CARBONATE, DIBUTYL LAUROYL GLUTAMIDE, DIBUTYL ETHYLHEXANOYL GLUTAMIDE, ACRYLATES COPOLYMER, SILICA SILYLATE, LITSEA CUBEBA FRUIT OIL, CITRUS AURANTIUM DULCIS (ORANGE) PEEL OIL, LAVANDULA ANGUSTIFOLIA (LAVENDER) OIL, DEHYDROACETIC ACID, PELARGONIUM GRAVEOLENS OIL, CANARIUM LUZONICUM GUM NONVOLATILES, EUCALYPTUS GLOBULUS LEAF OIL, ROSMARINUS OFFICINALIS (ROSEMARY) LEAF OIL, PENTAERYTHRITYL TETRA-DI-T-BUTYL HYDROXYHYDROCINNAMATE, ANTHEMIS NOBILIS FLOWER OIL, CITRUS AURANTIUM AMARA (BITTER ORANGE) FLOWER OIL, DIOSPYROS KAKI LEAF EXTRACT, GLYCERIN, AQUA/WATER/EAU, ECHIUM PLANTAGINEUM SEED OIL, CARDIOSPERMUM HALICACABUM FLOWER/LEAF/VINE EXTRACT, HELIANTHUS ANNUUS (SUNFLOWER) SEED OIL UNSAPONIFIABLES, PANCRATIUM MARITIMUM EXTRACT

PURPOSE

Sunscreen

WARNINGS

For external use only
Do not use on damaged or broken skin
When using this product keep out of eyes. Rinse with water to remove.
Stop use and ask a doctor if rash occurs
Keep out of reach of children. If product is swallowed, get medical help or contact a Poison Control Center right away.

KEEP OUT OF REACH OF CHILDREN

If product is swallowed, get medical help or contact a Poison Control Center right away.

Uses

• Helps prevent sunburn
• If used as directed with other sun protection measures
(see Directions), decreases the risk of skin cancer and early skin aging caused by the sun

Directions

• Apply liberally 15 minutes before sun exposure
• Reapply at least every 2 hours
• Use a water-resistant sunscreen if swimming or sweating
• Children under 6 months: Ask a doctor
• Sun Protection Measures. Spending time in the sun increases your risk of skin cancer and early skin aging.
To decrease this risk, regularly use a sunscreen with a Broad Spectrum SPF value of 15 or higher and other sun protection measures including:
• Limit time in the sun, especially from 10 a.m. ‒ 2 p.m.
• Wear long-sleeved shirts, pants, hats, and sunglasses

Other information

Protect this product from excessive heat and direct sun